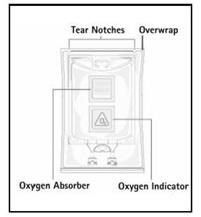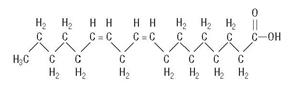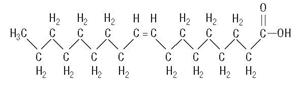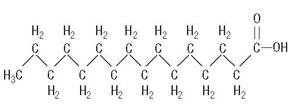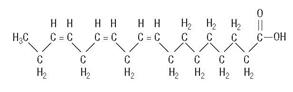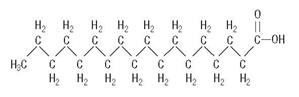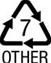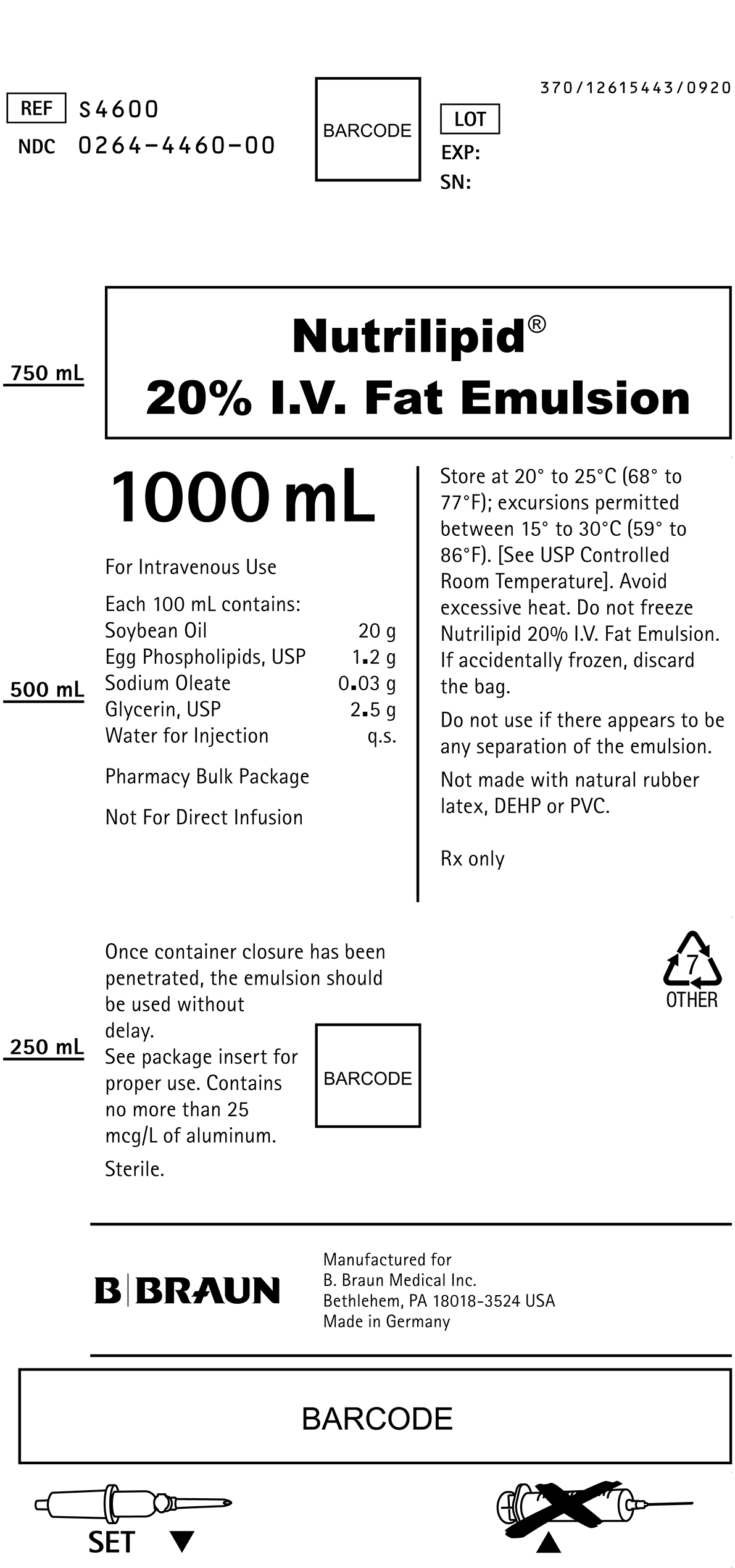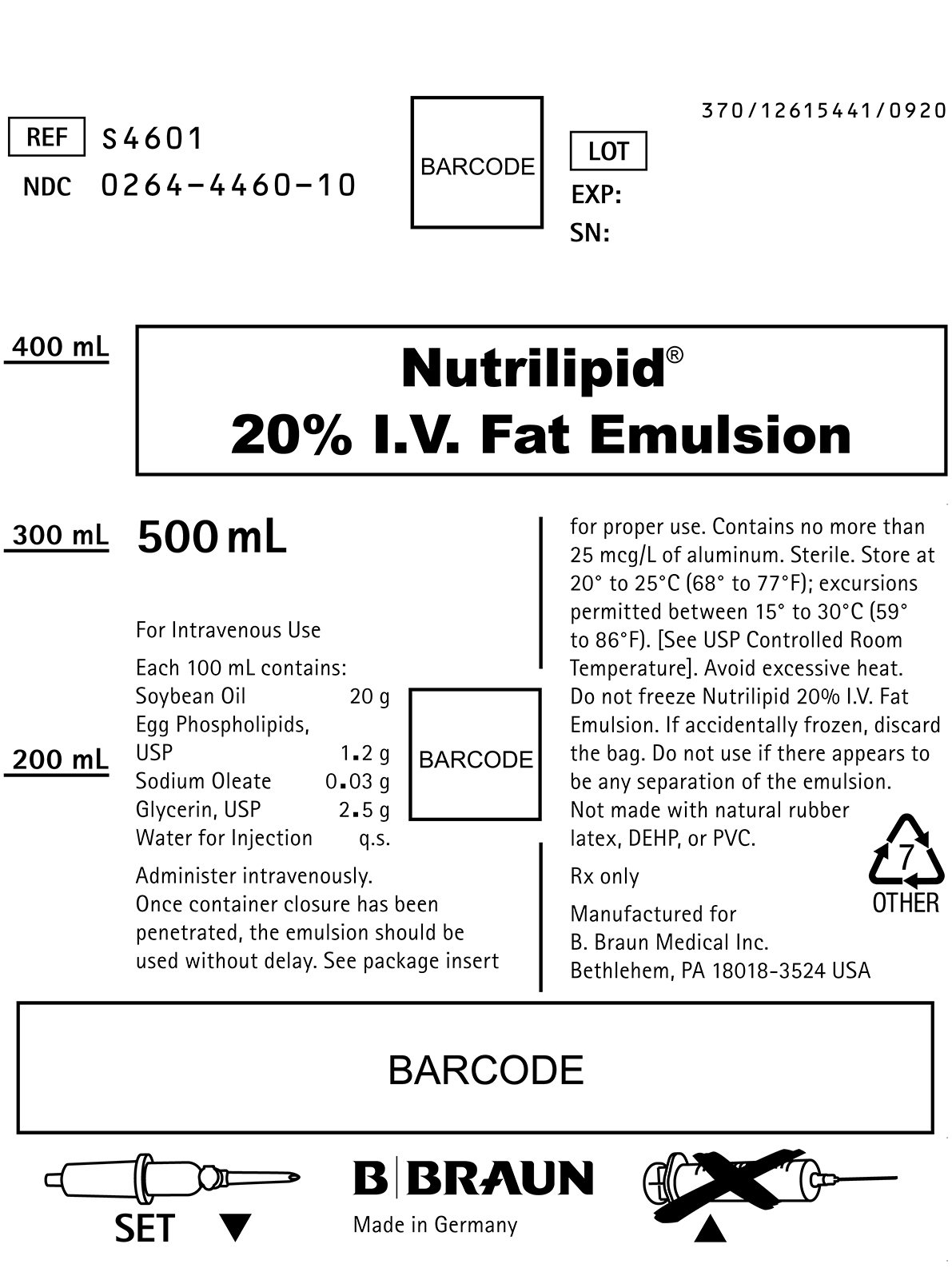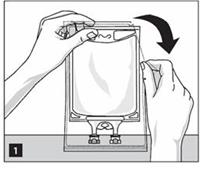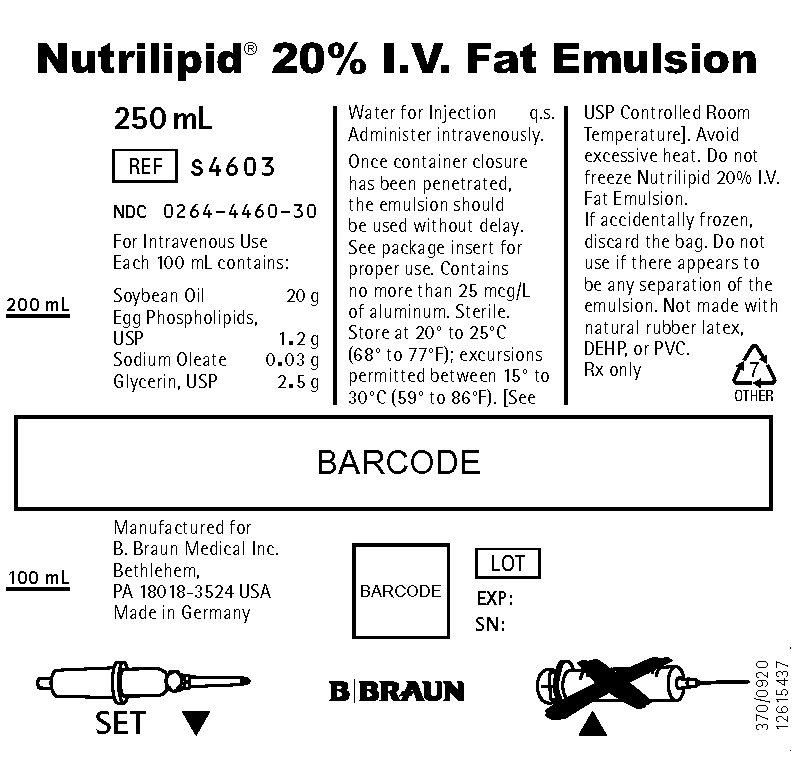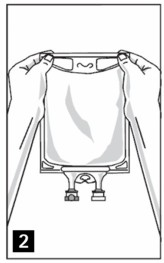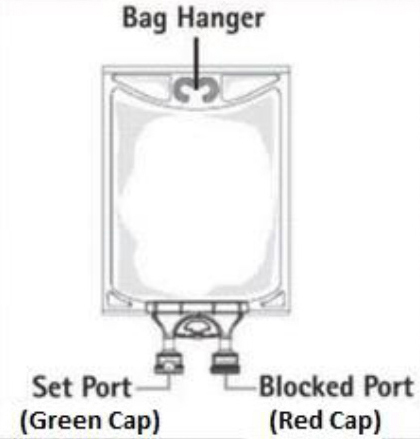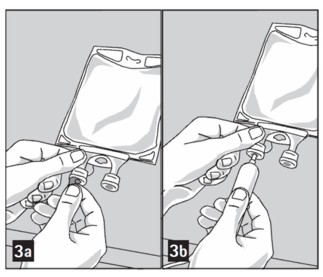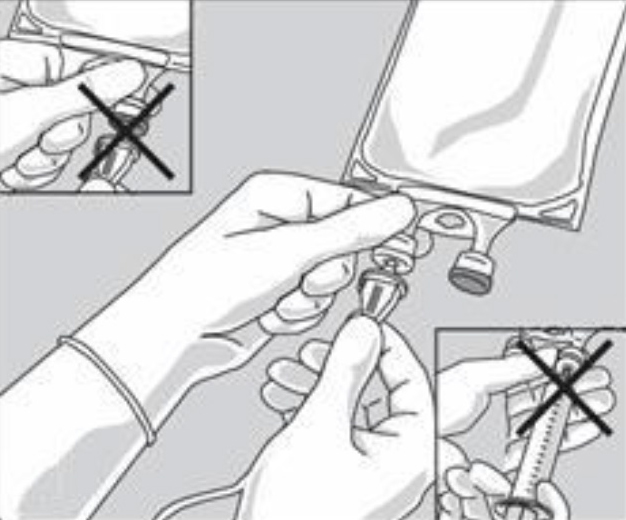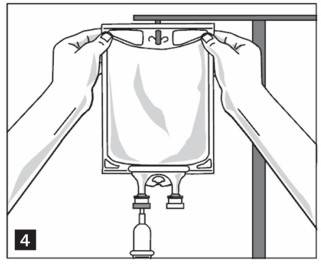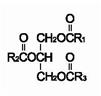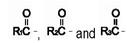 DRUG LABEL: NutriLipid I.V. Fat Emulsion
NDC: 0264-4460 | Form: INJECTION, SOLUTION
Manufacturer: B. Braun Medical Inc.
Category: prescription | Type: HUMAN PRESCRIPTION DRUG LABEL
Date: 20250724

ACTIVE INGREDIENTS: SOYBEAN OIL 20 g/100 mL
INACTIVE INGREDIENTS: WATER; EGG PHOSPHOLIPIDS 1.2 g/100 mL; GLYCERIN 2.5 g/100 mL; SODIUM OLEATE 0.03 g/100 mL; SODIUM HYDROXIDE

HIGHLIGHTS OF PRESCRIBING INFORMATION

These highlights do not include all the information needed to use NUTRILIPID 20% safely and effectively. See full prescribing information for NUTRILIPID 20%.
NUTRILIPID® 20% (lipid injectable emulsion), for intravenous use
Initial U.S. Approval: 1975

RECENT MAJOR CHANGES

Warnings and Precautions (5.3) 7/2025

1 INDICATIONS AND USAGE

Nutrilipid 20% is indicated as a source of calories and essential fatty acids for parenteral nutrition and as a source of essential fatty acids when a deficiency occurs when oral or enteral nutrition is not possible, insufficient, or contraindicated. (1)

2 DOSAGE AND ADMINISTRATION

- Nutrilipid 20% Pharmacy Bulk Package is not intended for direct intravenous administration. (2.1)
- For intravenous infusion through a peripheral or central line (2.1)
- Recommended dosage depends on age, energy expenditure, clinical status, body weight, tolerance, ability to metabolize and consideration of additional energy given to the patient. (2.4)
- For information on the age-appropriate infusion rate, see the full prescribing information. (2.4, 5.1)

Age | Nutritional Requirements
Age | Initial Recommended Dosage | Maximum Dosage
Preterm and term infants (<1 year) | 1 to 2 g/kg/day | 3 g/kg/day
Pediatric patients 1 to 10 years | 1 to 2 g/kg/day | 3 g/kg/day
Pediatric patients 11 to <17 years | 1 g/kg/day | 2.5 g/kg/day
Adults | 1 to 1.5 g/kg/day | 2.5 g/kg/day

3 DOSAGE FORMS AND STRENGTHS

Injectable emulsion:

- 20% (50 g/250 mL)(0.2 g/mL) of lipid in 250 mL single-dose flexible bag (3)
- 20% (100 g/500 mL)(0.2 g/mL) of lipid in 500 mL single-dose flexible bag (3)
- 20% (200 g/1,000 mL)(0.2 g/mL) of lipid in 1,000 mL Pharmacy Bulk Package (3)

4 CONTRAINDICATIONS

- Known hypersensitivity to egg, soybean, peanut, or any of the active or inactive ingredients. (4)
- Severe disorders of lipid metabolism characterized by hypertriglyceridemia (serum triglycerides >1,000 mg/dL). (4, 5.7)

5 WARNINGS AND PRECAUTIONS

- Clinical Decompensation with Rapid Infusion of Intravenous Lipid Emulsion in Neonates and Infants: Acute respiratory distress, metabolic acidosis, and death after rapid infusion of intravenous lipid emulsions have been reported. (5.1, 8.4)
- Parenteral Nutrition-Associated Liver Disease: Increased risk in patients who receive parenteral nutrition for greater than 2 weeks, especially preterm neonates. Monitor liver tests; if abnormalities occur, consider discontinuation or dosage reduction. (5.2, 8.4)
- Hypersensitivity reactions: Monitor for signs or symptoms. Discontinue infusion if reactions occur. (5.3)
- Infections, Fat Overload Syndrome, and Refeeding Syndrome, Hypertriglyceridemia: Monitor for signs and symptoms; monitor laboratory parameters. (5.4, 5.5, 5.6, 5.7)
- Aluminum Toxicity: Increased risk in patients with renal impairment, including preterm neonates. (5.8, 8.4)

6 ADVERSE REACTIONS

Adverse reactions include administration site reactions (e.g., erythema, extravasation, pain, phlebitis, pruritus, swelling), hyperlipidemia, hypercoagulability, thrombophlebitis, thrombocytopenia. (6)

To report SUSPECTED ADVERSE REACTIONS, contact B. Braun Medical Inc. at 1-833-425-1464 or FDA at 1-800-FDA-1088 or www.fda.gov/medwatch.

7 DRUG INTERACTIONS

Coumarin and coumarin derivatives, including warfarin: Anticoagulant activity may be counteracted; monitor laboratory parameters (7.1)

FULL PRESCRIBING INFORMATION

1 INDICATIONS AND USAGE

Nutrilipid® 20% is indicated as a source of calories and essential fatty acids for parenteral nutrition and as a source of essential fatty acids when a deficiency occurs when oral or enteral nutrition is not possible, insufficient, or contraindicated.

2 DOSAGE AND ADMINISTRATION

2.1 Administration Instructions

- Nutrilipid 20% Pharmacy Bulk Package is not intended for direct intravenous administration.
- Nutrilipid 20% is for intravenous infusion through a peripheral or central line. When administered with dextrose and amino acids, the choice of a central or peripheral venous route should depend on the osmolarity of the final infusate.
- Do not exceed the recommended maximum infusion rate in Table 1 [see Dosage and Administration (2.3) and Warnings and Precautions (5.1)].
- Use a non-vented infusion set or close the air vent on a vented set. Use of a vented intravenous administration set with the vent in the open position could result in air embolism.
- Use a dedicated line without any connections. Multiple connections could result in air embolism due to residual air being drawn from the primary container before administration of the fluid from the secondary container is completed.
- Use a 1.2 micron in-line filter.
- Nutrilipid 20% can be infused concurrently into the same vein as carbohydrate-amino acid solutions by means of a Y-connector located near the infusion site; flow rates of each solution should be controlled separately by infusion pumps.
- Do not use administration sets and lines that contain di-2-ethylhexyl phthalate (DEHP). Conventional administration sets contain polyvinyl chloride (PVC) components that have DEHP as a plasticizer.

2.2 Preparation Instructions for Nutrilipid 20% Bags for Direct Infusion

Caution: Nutrilipid 20% Pharmacy Bulk Package is not intended for direct intravenous administration.

Step 1: Inspect infusion bag overwrap and primary bag and do not use if damaged. Inspect oxygen indicator and do not use if oxygen indicator is pink or dark pink. Use only if container and seals are intact.

Step 2: To open, tear overwrap starting from the tear notches (Figure 1). Remove Nutrilipid 20% bag from overwrap and discard oxygen indicator, oxygen absorber and overwrap.

Step 3: Inspect Nutrilipid 20% bag visually (Figure 2). Nutrilipid 20% is a homogenous white and milky, sterile, nonpyrogenic lipid injectable emulsion. Parenteral drug products should be inspected visually for particulate matter and discoloration prior to administration, whenever solution and container permit. Inspect Nutrilipid 20% to ensure that the emulsion has not separated. Discard the bag if any particulates or discoloration are observed.

Step 4: Remove aluminum foil of outlet port at the bottom of the bag (Figure 3a) and attach administration set (Figure 3b).

Do not use/penetrate blocked port.

Step 5: Hang bag on IV Pole (Figure 4). If infusion pumps are used, flow rates of each parenteral fluid should be controlled with a separate pump.

Do not connect flexible bags in series to avoid air embolism due to possible residual gas contained in the primary bag.

Air embolism can result if residual gas in the bag is not fully evacuated prior to administration if the flexible bag is pressurized to increase flow rates.

If administration is controlled by a pumping device, discontinue pumping action before the bag runs dry to avoid air embolism.

2.3 Preparation Instructions for Admixing Using Total Parenteral Nutrition Pooling Bags

- Prepare the admixture into pooling bags using strict aseptic techniques to avoid microbial contamination.
- Do not add additives directly to Nutrilipid 20% Pharmacy Bulk Package.
  - Some additives may be incompatible and should not be used. If it is deemed advisable to introduce additives, prepare the admixture using strict aseptic techniques to avoid microbial contamination. Additions to the pooling bag should be evaluated by a pharmacist for compatibility. Questions about compatibility may be directed to B. Braun Medical Inc., Medical Affairs.
- Do not add Nutrilipid 20% to the pooling bag first; destabilization of the lipid may occur from such an admixture.
- The following proper mixing sequence must be followed to minimize pH related problems by ensuring that typically acidic Dextrose Injections are not mixed with lipid emulsions alone:

Manual Admixing

1. Manually transfer Dextrose Injection to the Total Parental Nutrition Admixture Container
2. Manually transfer Amino Acid Injection
3. Manually transfer Nutrilipid 20%

Use gentle agitation during admixing to minimize localized concentration effects; shake bags gently after each addition.

Automated Device Admixing

When admixing parenteral nutrition using an automated device, the Nutrilipid 20% must be separated from the dextrose product by an amino acid product or other non-acidic products.

- The prime destabilizers of emulsions are excessive acidity (such as pH below 5) and inappropriate electrolyte content. Give careful consideration to additions of divalent cations (Ca^++ and Mg^++), which have been shown to cause emulsion instability. Amino acid solutions exert buffering effects that protect the emulsion.
- Parenteral drug products should be inspected visually for particulate matter and discoloration prior to administration, whenever solution and container permit. Inspect Nutrilipid 20% to ensure that:
  - precipitates have not formed during the mixing or addition of additives and
  - the emulsion has not separated. Separation of the emulsion can be visibly identified by a yellowish streaking or the accumulation of yellowish droplets in the admixed emulsion.

Discard the admixture if any of the above are observed.

- If using an Automated Device, follow the manufacturer instructions.
- Use of the Pharmacy Bulk Package for admixing should be limited to up to four hours after opening.
- Admixtures should be used promptly with storage under refrigeration [2°C to 8°C (36°F to 46°F)] not to exceed 24 hours and must be completely used within 24 hours after removal from refrigeration.
- Do not connect flexible bags in series to avoid air embolism due to possible residual gas contained in the primary bag.
- Air embolism can result if residual gas in the bag is not fully evacuated prior to administration if the flexible bag is pressurized to increase flow rates.
- If administration is controlled by a pumping device, discontinue pumping action before the bag runs dry to avoid air embolism.
- Protect the admixed parenteral nutrition solution from light.

2.4 Dosing Considerations

The dosing of Nutrilipid 20% depends on the patient’s individual energy requirements, influenced by body weight, tolerance, clinical status, age-related growth rate in pediatric patients and the ability to eliminate and metabolize fat.

For partial parenteral nutrition, energy supply by oral or enteral nutrition has to be taken into account. For complete parenteral nutrition, concomitant supplementation with amino acids, carbohydrates, electrolytes, vitamins, and trace elements is necessary.

Prior to administration of Nutrilipid 20%, correct severe water and electrolyte disorders, severe fluid overload states, and severe metabolic disorders. Before starting the infusion, obtain serum triglyceride levels to establish the baseline value.

Recommended Adult and Pediatric Dosing

The recommended nutritional requirements of lipid and recommended dosages of Nutrilipid 20% to be administered to meet those requirements for adults and pediatric patients are provided in Table 1, along with recommendations for the initial and maximum infusion rates. The recommended duration of infusion for Nutrilipid 20% is between 12 and 24 hours, depending on the clinical situation. Adjust the administration flow rate by taking into account the dose being administered, the daily volume/intake, and the duration of the infusion [see Overdosage (10)].

Treatment with parenteral nutrition may be continued for as long as is required by the patient’s condition.

In patients with elevated triglyceride levels, initiate Nutrilipid 20% injection at a lower dose, and advance in smaller increments, monitoring the triglyceride levels with each adjustment [see Warnings and Precautions (5.7) and (5.9)].

When Nutrilipid 20% is administered to correct essential fatty acid deficiency, 8% to 10% of the caloric input should be supplied by Nutrilipid 20% in order to provide adequate amounts of linoleic and linolenic acids.

Table 1: Recommended Pediatric and Adult Dosage and Infusion Rate

Age | Nutritional Requirements | Direct Infusion Rate [Nutrilipid 20% Pharmacy Bulk Package is not intended for direct intravenous administration.]
Age | Recommended Initial Dosage and Maximum Dosage | Initial | Maximum
Preterm and term infants (less than 1 year of age); [see Warnings and Precautions (5.1)] | Initial 1 to 2 g/kg/day; not to exceed 3 g/kg/day [Daily dosage should also not exceed a maximum of 60% of total energy requirements [see Overdosage (10)].] | 0.05 mL/min for the first 10 to 15 minutes; gradually increase to the required rate after 15 minutes | 0.75 mL/kg/hour
Pediatric patients 1 to 10 years of age | Initial 1 to 2 g/kg/day; not to exceed 3 g/kg/day | 0.05 mL/min for the first 10 to 15 minutes; gradually increase to the required rate after 15 minutes | 0.75 mL/kg/hour
Pediatric patients 11 to <17 years of age | Initial 1 g/kg/day; not to exceed 2.5 g/kg/day | 0.05 mL/min for the first 10 to 15 minutes; gradually increase to the required rate after 15 minutes | 0.5 mL/kg/hour
Adults | 1 to 1.5 g/kg/day; not to exceed 2.5 g/kg/day | 0.5 mL/min for the first 15 to 30 minutes; gradually increase to the required rate after 30 minutes | 0.5 mL/kg/hour

3 DOSAGE FORMS AND STRENGTHS

Nutrilipid 20% is a homogenous white and milky, sterile, nonpyrogenic lipid injectable emulsion supplied as:

- 20% (50 g/250 mL) (0.2 g/mL) of lipid in 250 mL single-dose flexible bag
- 20% (100 g/500 mL) (0.2 g/mL) of lipid in 500 mL single-dose flexible bag
- 20% (200 g/1,000 mL) (0.2 g/mL) of lipid in 1,000 mL Pharmacy Bulk Package

4 CONTRAINDICATIONS

Nutrilipid 20% injection is contraindicated in patients who have:

- Known hypersensitivity to egg, soybean, peanut, or any of the active or inactive ingredients in Nutrilipid 20% [see Warnings and Precautions (5.3)].

- Severe disorders of lipid metabolism characterized by hypertriglyceridemia (serum triglyceride >1,000 mg/dL) [see Warnings and Precautions (5.7)].

5 WARNINGS AND PRECAUTIONS

5.1 Clinical Decompensation with Rapid Infusion of Intravenous Lipid Emulsion in Neonates and Infants

In the postmarketing setting, serious adverse reactions including acute respiratory distress, metabolic acidosis, and death have been reported in neonates and infants after rapid infusion of intravenous lipid emulsions. Hypertriglyceridemia was commonly reported.

Strictly adhere to the recommended total daily dosage; the hourly infusion rate should not exceed 0.75 mL/kg/hour [see Dosage and Administration (2.4)].

Preterm and small for gestational age infants have poor clearance of intravenous lipid emulsion and increased free fatty acid plasma levels following lipid emulsion infusion.

Carefully monitor the infant’s ability to eliminate the infused lipids from the circulation (e.g., measure serum triglycerides and/or plasma free fatty acid levels). If signs of poor clearance of lipids from the circulation occur, stop the infusion and initiate a medical evaluation [see Warnings and Precautions (5.5, 5.7) and Overdosage (10)].

5.2 Parenteral Nutrition-Associated Liver Disease and Other Hepatobiliary Disorders

Risk of Parenteral Nutrition-Associated Liver Disease

Parenteral nutrition-associated liver disease (PNALD), also referred to as intestinal failure-associated liver disease (IFALD), can present as cholestasis or hepatic steatosis, and may progress to steatohepatitis with fibrosis and cirrhosis (possibly leading to chronic hepatic failure). The etiology of PNALD is multifactorial; however, intravenously administered phytosterols (plant sterols) contained in plant-derived lipid emulsions, including Nutrilipid 20%, have been associated with development of PNALD.

Monitor liver tests in patients treated with Nutrilipid 20% and consider discontinuation or dosage reduction if abnormalities occur.

Other Hepatobiliary Disorders

Hepatobiliary disorders including cholecystitis and cholelithiasis have developed in some PN-treated patients without preexisting liver disease.

Monitor liver tests when administering Nutrilipid 20%. Patients developing signs of hepatobiliary disorders should be assessed early to determine whether these conditions are related to Nutrilipid 20% use.

5.3 Hypersensitivity Reactions

Nutrilipid 20% contains soybean oil and egg phospholipids which may cause hypersensitivity reactions. Cross reactions have been observed between soybean and peanut. In postmarketing experience, anaphylaxis has been reported following Nutrilipid administration [see Adverse Reactions (6.2)].

Nutrilipid 20% is contraindicated in patients with known hypersensitivity to egg, soybean, peanut, or any of the active or inactive ingredients in Nutrilipid 20% [see Contraindications (4)]. If a hypersensitivity reaction occurs, stop infusion of Nutrilipid 20% immediately and initiate appropriate treatment and supportive measures.

5.4 Infections

Lipid emulsions, such as Nutrilipid 20%, can support microbial growth and are an independent risk factor for the development of catheter-related bloodstream infections. To decrease the risk of infectious complications, ensure aseptic techniques are used for catheter placement, catheter maintenance, and preparation and administration of Nutrilipid 20%.

Monitor for signs and symptoms of infection, including fever and chills, as well as including laboratory test results (including leukocytosis and hyperglycemia). Perform frequent checks of the intravenous catheter insertion site for edema, redness, and discharge.

5.5 Fat Overload Syndrome

Fat overload syndrome is a rare condition that has been reported with intravenous lipid formulations and is characterized by a sudden deterioration in the patient's condition (e.g., fever, anemia, leukopenia, thrombocytopenia, coagulation disorders, hyperlipidemia, hepatomegaly, deteriorating liver function, and central nervous system manifestations such as coma). A reduced or limited ability to metabolize lipids, accompanied by prolonged plasma clearance (resulting in higher lipid levels), may result in this syndrome. Although fat overload syndrome has been most frequently observed when the recommended lipid dose or infusion rate was exceeded, cases have also been described when the lipid formulation was administered according to instructions.

If signs or symptoms of fat overload syndrome occur, stop Nutrilipid 20%. The syndrome is usually reversible when the infusion of the lipid emulsion is stopped.

5.6 Refeeding Syndrome

Administering PN to severely malnourished patients may result in the refeeding syndrome, which is characterized by the intracellular shift of potassium, phosphorus, and magnesium as the patient becomes anabolic. Thiamine deficiency and fluid retention may also develop. To prevent these complications, closely monitor severely malnourished patients and slowly increase their nutrient intake.

5.7 Hypertriglyceridemia

The use of Nutrilipid 20% is contraindicated in patients with hypertriglyceridemia with serum triglyceride concentrations >1,000 mg/dL.

Patients with conditions such as inherited lipid disorders, obesity, diabetes mellitus, or metabolic syndromes have a higher risk of developing hypertriglyceridemia with the use of Nutrilipid 20%. In addition, patients with hypertriglyceridemia may have worsening of their hypertriglyceridemia with administration of Nutrilipid 20%. Excessive dextrose administration may further increase such risk.

Evaluate patients’ capacity to metabolize and eliminate the infused lipid emulsion by measuring serum triglycerides before the start of infusion (baseline value) and regularly throughout treatment. If triglyceride levels are above 400 mg/dL in adults, stop the Nutrilipid 20% infusion and monitor serum triglyceride levels to avoid clinical consequences of hypertriglyceridemia such as pancreatitis. In pediatric patients with hypertriglyceridemia, lower triglyceride levels (i.e., below 400 mg/dL) may be associated with adverse reactions. Monitor serum triglyceride levels to avoid potential complications with hypertriglyceridemia such as pancreatitis, lipid pneumonitis, and neurologic changes, including kernicterus.

To minimize the risk of new or worsening of hypertriglyceridemia, assess high-risk patients for their overall energy intake including other sources of lipids and dextrose, as well as concomitant drugs that may affect lipid and dextrose metabolism.

5.8 Aluminum Toxicity

Nutrilipid 20% contains no more than 25 mcg/L of aluminum.

Prolonged parenteral nutrition administration in patients with renal impairment may result in aluminum reaching toxic levels. Preterm infants are at greater risk because their kidneys are immature, and they require large amounts of calcium and phosphate solutions that contain aluminum.

Patients with impaired kidney function, including preterm infants, who receive parenteral levels of aluminum at greater than 4 to 5 mcg/kg/day, accumulate aluminum at levels associated with central nervous system and bone toxicity. Tissue loading may occur at even lower rates of administration of total parenteral nutrition products.

5.9 Monitoring / Laboratory Tests

Monitor fluid status closely in patients with pulmonary edema or heart failure.

Throughout treatment, monitor serum triglycerides [see Warnings and Precautions (5.7)], fluid and electrolyte status, serum osmolarity, blood glucose, liver and kidney function, blood count (including platelets), and coagulation parameters.

The lipids contained in Nutrilipid may interfere with some laboratory tests (e.g., hemoglobin, lactate dehydrogenase, bilirubin, oxygen saturation) if blood is sampled before the lipids have cleared from the bloodstream. Conduct these tests at least 6 hours after stopping the infusion.

Nutrilipid contains Vitamin K that may counteract anticoagulant activity [see Drug Interactions (7)].

6 ADVERSE REACTIONS

Adverse Reactions described elsewhere in labeling:

- Clinical Decompensation with Rapid Infusion of Intravenous Lipid Emulsion in Neonates and Infants [see Warnings and Precautions (5.1)]
- Risk of Parenteral Nutrition Associated Liver Disease [see Warnings and Precautions (5.2)]
- Hypersensitivity Reactions [see Warnings and Precautions (5.3)]
- Infections [see Warnings and Precautions (5.4)]
- Fat Overload Syndrome [see Warnings and Precautions (5.5)]
- Refeeding Syndrome [see Warnings and Precautions (5.6)]
- Hypertriglyceridemia [see Warnings and Precautions (5.7)]
- Aluminum Toxicity [see Warnings and Precautions (5.8)]

6.1 Clinical Trials Experience

Because clinical trials are conducted under widely varying conditions, adverse reaction rates observed in the clinical trials of a drug cannot be directly compared to rates in the clinical trials of another drug and may not reflect the rates observed in practice.

Adverse reactions reported with other intravenous lipid emulsions include hyperlipidemia, hypercoagulability, thrombophlebitis, and thrombocytopenia.

Adverse reactions reported in long-term use with other intravenous lipid emulsions include hepatomegaly, jaundice due to central lobular cholestasis, splenomegaly, thrombocytopenia, leukopenia, abnormalities in liver function tests, brown pigmentation of the liver and overloading syndrome (focal seizures, fever, leukocytosis, hepatomegaly, splenomegaly and shock).

6.2 Postmarketing Experience

The following adverse reactions have been identified during post-approval use of Nutrilipid 20%. Because these reactions are reported voluntarily from a population of uncertain size, it is not always possible to reliably estimate their frequency or establish a causal relationship to drug exposure.

General disorders and administration site conditions: extravasation, infusion site erythema, infusion site pain, infusion site phlebitis, infusion site pruritus, and infusion site swelling.

Immune system disorders: hypersensitivity reactions, including anaphylaxis [see Contraindications (4), Warnings and Precautions (5.3)].

7 DRUG INTERACTIONS

7.1 Coumarin and Coumarin Derivatives

The soybean oil in Nutrilipid 20% contains vitamin K1. Vitamin K can reverse the anticoagulant activity of coumarin and coumarin derivatives, including warfarin, which work by blocking recycling of vitamin K. Monitor laboratory parameters for anticoagulant activity in patients who are on both Nutrilipid 20% and coumarin or coumarin derivatives.

8 USE IN SPECIFIC POPULATIONS

8.1 Pregnancy

Risk Summary

There are no adequate or well controlled studies with Nutrilipid 20% in pregnant women. Additionally, animal reproduction studies have not been conducted with Nutrilipid 20%. It is not known whether Nutrilipid 20% can cause fetal harm when administered to a pregnant woman. Nutrilipid 20% should be given to a pregnant woman only if clearly needed.

8.3 Nursing Mothers

It is not known whether Nutrilipid 20% is present in human milk. Because many drugs are present in human milk, caution should be exercised when Nutrilipid 20% is administered to a nursing woman.

8.4 Pediatric Use

The evidence for safety and efficacy in pediatric patients of Nutrilipid 20% as a source of calories and essential fatty acids for parenteral nutrition and as a source of essential fatty acids when a deficiency occurs when oral or enteral nutrition is not possible, insufficient, or contraindicated is derived from the published literature and clinical experience with similar soybean oil-based intravenous lipid emulsions.

In the postmarketing setting, clinical decompensation with rapid infusion of intravenous lipid emulsion in neonates and infants, sometimes fatal, has been reported [see Warnings and Precautions (5.1)]. Patients, particularly preterm infants, are at risk for aluminum toxicity [see Warnings and Precautions (5.9)]. Patients, including pediatric patients, may be at risk for PNALD [see Warnings and Precautions (5.2)]. In clinical trials of a pure soybean oil based intravenous lipid emulsion product, thrombocytopenia in neonates occurred (less than 1%).

8.5 Geriatric Use

Clinical studies of Nutrilipid 20% did not include sufficient numbers of subjects aged 65 and over to determine whether they respond differently from younger subjects. Other reported clinical experience has not identified differences in responses between the elderly and younger patients. In general, dose selection for an elderly patient should be cautious, usually starting at the low end of the dosing range, reflecting the greater frequency of decreased hepatic, renal, or cardiac function, and of concomitant disease or other drug therapy.

10 OVERDOSAGE

In the event of overdose, serious adverse reactions may result [see Warnings and Precautions (5.1, 5.5)]. Stop the infusion to allow lipids to clear from serum. The effects are usually reversible after the lipid infusion is stopped. If medically appropriate, further intervention may be indicated. The lipid administered and fatty acids produced are not dialyzable.

11 DESCRIPTION

Nutrilipid 20% is a homogenous white and milky sterile, nonpyrogenic lipid emulsion for intravenous administration.

Each 100 mL of Nutrilipid 20% contains: Soybean Oil 20 g; Egg Yolk Phospholipid 1.2 g; Glycerin USP (glycerol) 2.5 g; Sodium Oleate 0.03 g; Water for Injection USP qs.

pH adjusted with Sodium Hydroxide NF.

pH: 6.8 (6.0-8.9); Osmolality: 390 mOsmol/kg (actual). Contains emulsified fat particles averaging approximately 0.26 micron in diameter, similar to naturally occurring chylomicrons. The total caloric value, including fat, phospholipid, and glycerol is 2.0 Kcal per mL.

Soybean oil is a refined natural product consisting of a mixture of neutral triglycerides of predominantly unsaturated fatty acids with the following structure:

are saturated and unsaturated fatty acid residues. The major component fatty acids are linoleic (48% - 58%), oleic (17% - 30%), palmitic (9% -13%), linolenic (4% - 11%), and stearic (2.5% - 5.0%). These fatty acids have the folIowing chemical and structural formulas:

Linoleic Acid

C18H32O2

Oleic Acid

C18H34O2

Palmitic Acid

C16H32O2

Linolenic Acid

C18H30O2

Stearic Acid

C18H36O2

Egg yolk phospholipids are a mixture of naturally occurring phospholipids isolated from egg yolk.

Glycerol is chemically designated C3H8O3 and is a clear colorless, hygroscopic syrupy liquid. It is added to adjust tonicity.

Not made with natural rubber latex, PVC or DEHP.

Drug product contains no more than 25 mcg/L of aluminum.

12 CLINICAL PHARMACOLOGY

12.1 Mechanism of Action

Nutrilipid 20% administered intravenously provides biologically utilizable source of calories and essential fatty acids.

Fatty acids serve as an important substrate for energy production. The most common mechanism of action for energy production derived from fatty acid metabolism is beta oxidation. Fatty acids are important for membrane structure and function, precursors for bioactive molecules (such as prostaglandins), and as regulators of gene expression.

Nutrilipid 20% causes an increase in heat production, decrease in respiratory quotient, and increase in oxygen consumption following its administration.

12.3 Pharmacokinetics

The infused lipid particles are removed from the bloodstream in a manner generally thought to be similar to the enzymatic clearance of naturally produced chylomicrons formed after enteral fat intake. Following infusion, there is a transient increase in plasma triglycerides. The triglycerides are hydrolyzed to free fatty acids and glycerol by the enzyme lipoprotein lipase. The free fatty acids either enter the tissues (where they may be oxidized or resynthesized into triglycerides and stored) or circulate in the plasma, bound to albumin. In the liver, circulating free fatty acids are oxidized or converted to very low-density lipoproteins that re-enter the bloodstream.

Phosphatides are the hydrophobic components of membranes and provide electrically insulated layers. They are involved in the formation of membrane structures. Choline prevents deposition of fat in the liver.

Glycerol is metabolized to carbon dioxide and glycogen or is used in the synthesis of body fats.

13 NONCLINICAL TOXICOLOGY

13.1 Carcinogenesis, Mutagenesis, Impairment of Fertility

Long-term animal studies have not been conducted to evaluate the carcinogenic potential of Nutrilipid 20%, or its effects on fertility. Genotoxic studies have not been conducted with Nutrilipid 20% to assess its mutagenic potential.

16 HOW SUPPLIED/STORAGE AND HANDLING

Nutrilipid 20% is supplied as a homogenous white and milky, sterile, nonpyrogenic, lipid injectable emulsion in the following strengths:

Strengths | REF | Volume | NDC Number
20% (50 g/250 mL) (0.2 g/mL) | S4603 | 250 mL | 0264-4460-30
20% (100 g/500 mL) (0.2 g/mL) | S4601 | 500 mL | 0264-4460-10
20% (200 g/1,000 mL) (0.2 g/mL) | S4600 | 1,000 mL | 0264-4460-00 (Pharmacy Bulk Container)

Do not freeze. If accidentally frozen, discard the container.

Store at 20°C to 25°C (68°F to 77°F); excursions permitted between 15°C to 30°C (59°F to 86°F). [See USP Controlled Room Temperature].

Use of the Pharmacy Bulk Package for admixing should be limited to up to four hours after opening. Admixtures should be used promptly with storage under refrigeration [2°C to 8°C (36°F to 46°F)] not to exceed 24 hours and must be completely used within 24 hours after removal from refrigeration.

17 PATIENT COUNSELING INFORMATION

When initiating Nutrilipid 20% administration, discuss the following information with the patient or caregiver:

Clinical Decompensation with Rapid Infusion of Intravenous Lipid Emulsion in Neonates and Infants

Inform caregivers that acute respiratory distress and death may occur in neonates and infants after rapid infusion of intravenous lipid emulsions. If Nutrilipid is infused at home, instruct caregivers not to exceed maximum infusion rate [see Warnings and Precautions (5.1)].

Parenteral Nutrition-Associated Liver Disease and Other Hepatobiliary Disorders

Inform patients and caregivers that use of parenteral nutrition may result in parenteral nutrition-associated liver disease and/or other hepatobiliary disorders [see Warnings and Precautions (5.2)].

Hypersensitivity Reactions

Inform patients and caregivers that Nutrilipid 20% may cause hypersensitivity reactions, including anaphylaxis. If Nutrilipid 20% is infused at home, instruct patients and caregivers to stop the infusion of Nutrilipid 20% immediately and seek medical attention if they experience signs or symptoms of a hypersensitivity reaction, such as rapid or weak heartbeat, feeling faint, difficulty in breathing or swallowing, vomiting, nausea, headache, sweating, dizziness, hives, rash, itching, flushing, dizziness, fever, or chills [see Warnings and Precautions (5.3)].

Infections

Inform patients and caregivers that patients who receive Nutrilipid 20% are at risk of infection. If Nutrilipid 20% is infused at home, instruct patients and caregivers to ensure aseptic techniques are used for the preparation and administration of Nutrilipid 20% and to monitor for signs and symptoms of infection [see Warnings and Precautions (5.4)].

Fat Overload Syndrome

Inform patients and caregivers that fat overload syndrome has been reported with the use of intravenous lipid emulsions. If Nutrilipid 20% is infused at home, instruct patients and caregivers to stop Nutrilipid 20% if signs or symptoms of fat overload syndrome occur [see Warnings and Precautions (5.5)].

Refeeding Syndrome

If the patient is severely malnourished, inform patients and caregivers that administering parenteral nutrition including Nutrilipid 20% may result in refeeding syndrome [see Warnings and Precautions (5.6)].

Hypertriglyceridemia

Inform patients and caregivers about the risks of hypertriglyceridemia with Nutrilipid 20% use [see Warnings and Precautions (5.7)].

Aluminum Toxicity

Inform patients and caregivers that prolonged PN administration in patients with renal impairment, including preterm neonates, may result in aluminum reaching toxic levels associated with central nervous system and bone toxicity [see Warnings and Precautions (5.8)].

Preparation and Administration Instructions

If it is acceptable for a patient and caregiver to administer Nutrilipid 20% at home, then provide recommendations on how to prepare, administer, and store Nutrilipid 20% [see Dosage and Administration (2.1, 2.2)].

Nutrilipid 20% is a registered trademark of B. Braun Melsungen AG.

Rx only

Manufactured for
B. Braun Medical Inc.
Bethlehem, PA 18018-3524 USA
1-800-227-2862

Made in Germany

LD-217-6

PRINCIPAL DISPLAY PANEL - 1000 mL

REF S4600
NDC 0264-4460-00

LOT
EXP:
SN:

Nutrilipid®
20% I.V. Fat Emulsion

1000 mL

For Intravenous Use

Each 100 mL contains:
Soybean Oil 20 g
Egg Phospholipids, USP 1.2 g
Sodium Oleate 0.03 g
Glycerin, USP 2.5 g
Water for Injection q.s.

Pharmacy Bulk Package

Not For Direct Infusion

Once container closure has been penetrated, the emulsion should be used without delay.

See package insert for proper use. Contains no more than 25 mcg/L of aluminum.

Sterile.

Store at 20° to 25°C (68° to 77°F); excursions permitted between 15° to 30°C (59° to 86°F). [See USP Controlled Room Temperature]. Avoid excessive heat. Do not freeze Nutrilipid 20% I.V. Fat Emulsion. If accidentally frozen, discard the bag.

Do not use if there appears to be any separation of the emulsion.

Not made with natural rubber latex, DEHP or PVC.

Rx only

Manufactured for
B. Braun Medical Inc.
Bethlehem, PA 18018-3524 USA
Made in Germany

SET

370/12615443/0920

PRINCIPAL DISPLAY PANEL - 500 mL

REF S4601
NDC 0264-4460-10

LOT
EXP:
SN:

Nutrilipid®
20% I.V. Fat Emulsion

500 mL

For Intravenous Use

Each 100 mL contains:
Soybean Oil 20 g
Egg Phospholipids, USP 1.2 g
Sodium Oleate 0.03 g
Glycerin, USP 2.5 g
Water for Injection q.s.

Administer intravenously.

Once container closure has been penetrated, the emulsion should be used without delay. See package insert for proper use. Contains no more than 25 mcg/L of aluminum. Sterile. Store at 20° to 25°C (68° to 77°F); excursions permitted between 15° to 30°C (59° to 86°F). [See USP Controlled Room Temperature]. Avoid excessive heat. Do not freeze Nutrilipid 20% I.V. Fat Emulsion. If accidentally frozen, discard the bag. Do not use if there appears to be any separation of the emulsion.

Not made with natural rubber latex, DEHP, or PVC.

Rx only

Manufactured for
B. Braun Medical Inc.
Bethlehem, PA 18018-3524 USA
Made in Germany

SET

370/12615441/0920

PRINCIPAL DISPLAY PANEL - 250 mL

Nutrilipid® 20% I.V. Fat Emulsion

250 mL
REF S4603

NDC 0264-4460-30

For Intravenous Use
Each 100 mL contains:

Soybean Oil 20 g
Egg Phospholipids, USP 1.2 g
Sodium Oleate 0.03 g
Glycerin, USP 2.5 g
Water for Injection q.s.
Administer intravenously.

Once container closure has been penetrated, the emulsion should be used without delay. See package insert for proper use. Contains no more than 25 mcg/L of aluminum. Sterile. Store at 20° to 25°C (68° to 77°F); excursions permitted between 15° to 30°C (59° to 86°F). [See USP Controlled Room Temperature]. Avoid excessive heat. Do not freeze Nutrilipid 20% I.V. Fat Emulsion.

If accidentally frozen, discard the bag. Do not use if there appears to be any separation of the emulsion. Not made with natural rubber latex, DEHP, or PVC.

Rx only

Manufactured for
B. Braun Medical Inc.
Bethlehem, PA 18018-3524 USA
Made in Germany

LOT
EXP:
SN:

SET

370/0920
12615437